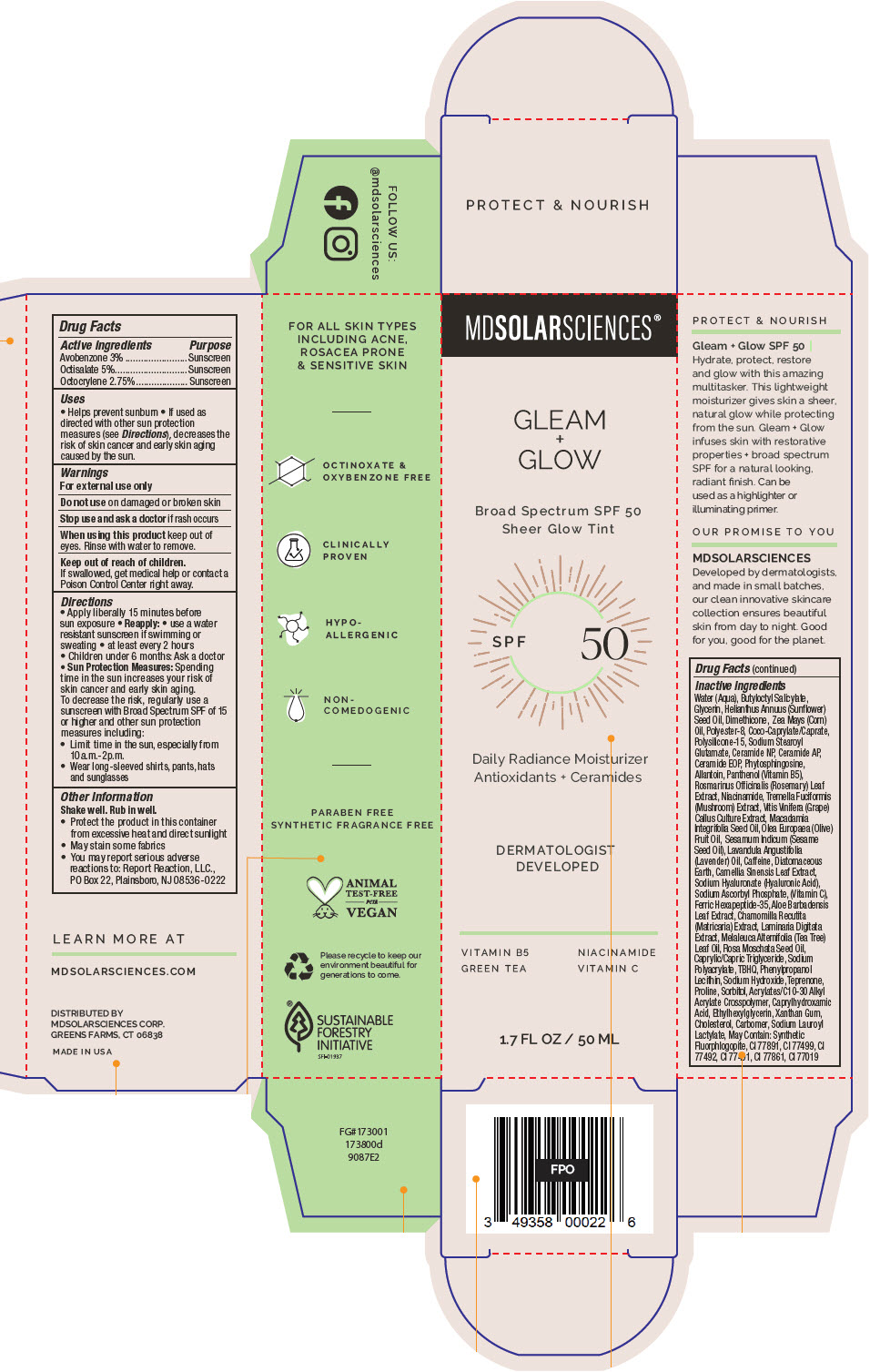 DRUG LABEL: Gleam plus Glow SPF 50.
NDC: 49358-581 | Form: LOTION
Manufacturer: MDSolarSciences
Category: otc | Type: HUMAN OTC DRUG LABEL
Date: 20250605

ACTIVE INGREDIENTS: AVOBENZONE 30 mg/1 mL; OCTISALATE 50 mg/1 mL; OCTOCRYLENE 27.5 mg/1 mL
INACTIVE INGREDIENTS: WATER; BUTYLOCTYL SALICYLATE; GLYCERIN; HELIANTHUS ANNUUS FLOWERING TOP; DIMETHICONE; CORN OIL; POLYESTER-8 (1400 MW, CYANODIPHENYLPROPENOYL CAPPED); COCOYL CAPRYLOCAPRATE; POLYSILICONE-15; SODIUM STEAROYL GLUTAMATE; CERAMIDE NP; CERAMIDE AP; CERAMIDE 9; PHYTOSPHINGOSINE; ALLANTOIN; PANTHENOL; ROSEMARY; NIACINAMIDE; TREMELLA FUCIFORMIS FRUITING BODY; VITIS VINIFERA SEED; MACADAMIA OIL; OLIVE OIL; SESAME OIL; LAVENDER OIL; CAFFEINE; DIATOMACEOUS EARTH; GREEN TEA LEAF; HYALURONATE SODIUM; SODIUM ASCORBYL PHOSPHATE; ACETYL HEXAPEPTIDE-8; ALOE VERA LEAF; CHAMOMILE; LAMINARIA DIGITATA; TEA TREE OIL; ROSA MOSCHATA SEED OIL; MEDIUM-CHAIN TRIGLYCERIDES; SODIUM POLYACRYLATE (8000 MW); TERT-BUTYLHYDROQUINONE; PHENYLPROPANOL; HYDROGENATED SOYBEAN LECITHIN; SODIUM HYDROXIDE; TEPRENONE; PROLINE; SORBITOL; CARBOMER INTERPOLYMER TYPE A (ALLYL SUCROSE CROSSLINKED); CAPRYLHYDROXAMIC ACID; ETHYLHEXYLGLYCERIN; XANTHAN GUM; CHOLESTEROL; CARBOMER HOMOPOLYMER TYPE C (ALLYL PENTAERYTHRITOL CROSSLINKED); SODIUM LAUROYL LACTYLATE

Gleam + Glow SPF 50.
SPF 50 Broad Spectrum Sunscreen UVA-UVB Sheer Glow Tint

Drug Facts

ACTIVE INGREDIENT

Active ingredients | Purpose
Avobenzone 3% | Sunscreen
Octisalate 5% | Sunscreen
Octocrylene 2.75% | Sunscreen

Uses

- Helps prevent sunburn
- If used as directed with other sun protection measures (see Directions), decreases the risk of skin cancer and early skin aging caused by the sun.

Warnings

For external use only

Do not useon damaged or broken skin

Stop use and ask a doctorif rash occurs

WHEN USING

When using this productkeep out of eyes. Rinse with water to remove.

Keep out of reach of children.

If swallowed, get medical help or contact a Poison Control Center right away.

Directions

- Apply liberally 15 minutes before sun exposure
- Reapply:
  - use a water resistant sunscreen if swimming or sweating
  - at least every 2 hours
- Children under 6 months: Ask a doctor
- Sun Protection Measures:Spending time in the sun increases your risk of skin cancer and early skin aging. To decrease the risk, regularly use a sunscreen with Broad Spectrum SPF of 15 or higher and other sun protection measures including:
  - Limit time in the sun, especially from 10a.m.-2p.m.
  - Wear long-sleeved shirts, pants, hats and sunglasses

Other Information

Shake well. Rub in well.

- Protect the product in this container from excessive heat and direct sunlight
- May stain some fabrics
- You may report serious adverse reactions to: Report Reaction, LLC., PO Box 22, Plainsboro, NJ 08536-0222

Inactive Ingredients

Water (Aqua), Butyloctyl Salicylate, Glycerin, Helianthus Annuus (Sunflower) Seed Oil, Dimethicone, Zea Mays (Corn) Oil, Polyester-8, Coco-Caprylate/Caprate, Polysilicone-15, Sodium Stearoyl Glutamate, Ceramide NP, Ceramide AP, Ceramide EOP, Phytosphingosine, Allantoin, Panthenol (Vitamin B5), Rosmarinus Officinalis (Rosemary) Leaf Extract, Niacinamide, Tremella Fuciformis (Mushroom) Extract, Vitis Vinifera (Grape) Callus Culture Extract, Macadamia Integrifolia Seed Oil, Olea Europaea (Olive) Fruit Oil, Sesamum Indicum (Sesame Seed Oil), Lavandula Angustifolia (Lavender) Oil, Caffeine, Diatomaceous Earth, Camellia Sinensis Leaf Extract, Sodium Hyaluronate (Hyaluronic Acid), Sodium Ascorbyl Phosphate, (Vitamin C), Ferric Hexapeptide-35, Aloe Barbadensis Leaf Extract, Chamomilla Recutita (Matricaria) Extract, Laminaria Digitata Extract, Melaleuca Alternifolia (Tea Tree) Leaf Oil, Rosa Moschata Seed Oil, Caprylic/Capric Triglyceride, Sodium Polyacrylate, TBHQ, Phenylpropanol Lecithin, Sodium Hydroxide, Teprenone, Proline, Sorbitol, Acrylates/C10-30 Alkyl Acrylate Crosspolymer, Caprylhydroxamic Acid, Ethylhexylglycerin, Xanthan Gum, Cholesterol, Carbomer, Sodium Lauroyl Lactylate, May Contain: Synthetic Fluorphlogopite, CI 77891, CI 77499, CI 77492, CI 77491, CI 77861, CI 77019

DISTRIBUTED BY
MDSOLARSCIENCES CORP.
GREENS FARMS, CT 06838

PRINCIPAL DISPLAY PANEL - 50 ML Bottle Carton

MDSOLARSCIENCES®

GLEAM
+
GLOW

Broad Spectrum SPF 50
Sheer Glow Tint

SPF
50

Daily Radiance Moisturizer
Antioxidants + Ceramides

DERMATOLOGIST
DEVELOPED

VITAMIN B5
GREEN TEA

NIACINAMIDE
VITAMIN C

1.7 FL OZ / 50 ML